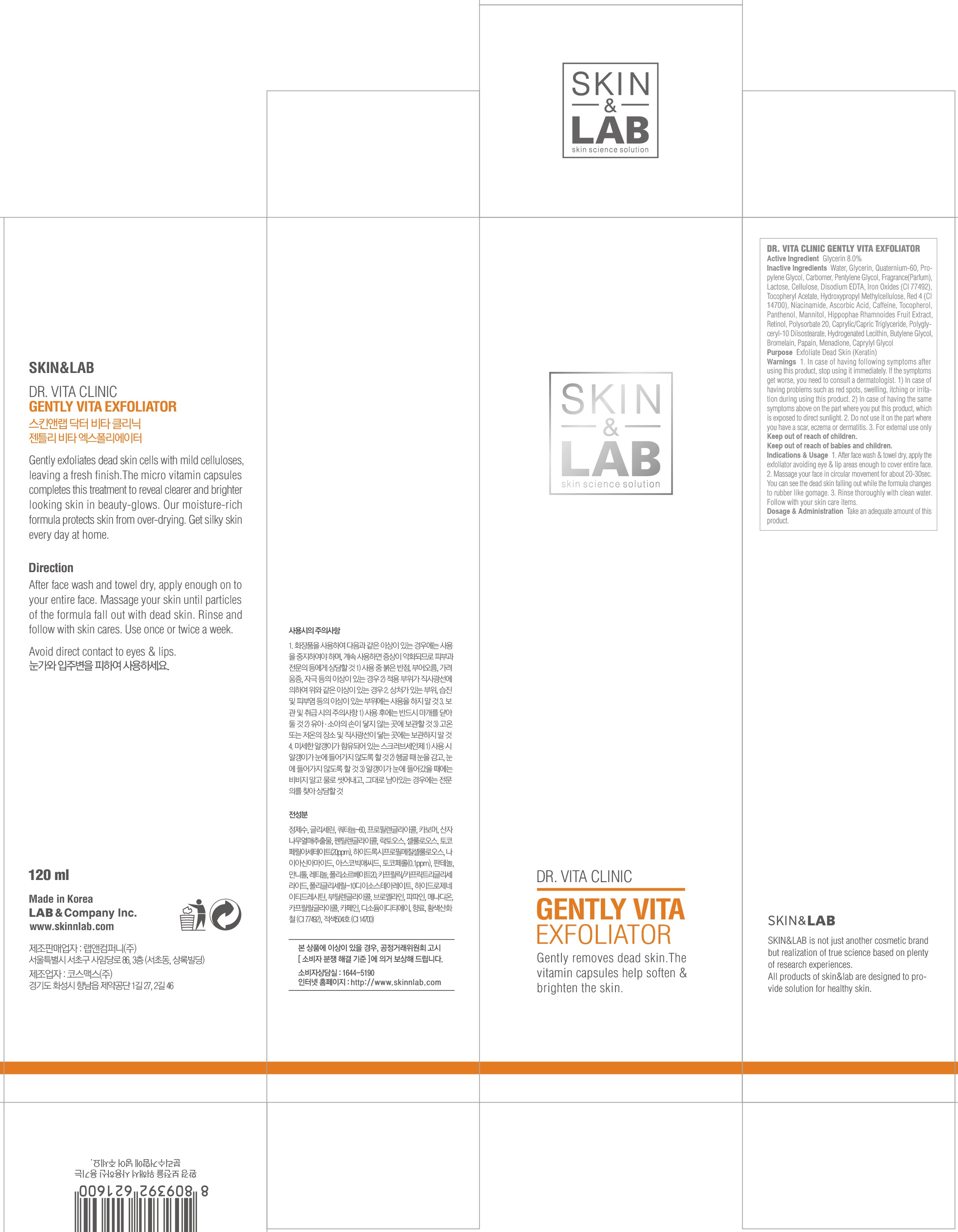 DRUG LABEL: Dr Vita Clinic Gently Vita Exfoliator
NDC: 69457-030 | Form: GEL
Manufacturer: LAB & Company Inc.
Category: otc | Type: HUMAN OTC DRUG LABEL
Date: 20160803

ACTIVE INGREDIENTS: Glycerin 9.6 g/120 mL
INACTIVE INGREDIENTS: Water; Propylene Glycol

ACTIVE INGREDIENT

Active Ingredient: Glycerin 8.0%

INACTIVE INGREDIENT

Inactive Ingredients: Water, Quaternium-60, Propylene Glycol, Carbomer, Pentylene Glycol, Fragrance(Parfum), Lactose, Cellulose, Disodium EDTA, Iron Oxides (CI 77492), Tocopheryl Acetate, Hydroxypropyl Methylcellulose, Red 4 (CI 14700), Niacinamide, Ascorbic Acid, Caffeine, Tocopherol, Panthenol, Mannitol, Hippophae Rhamnoides Fruit Extract, Retinol, Polysorbate 20, Caprylic/Capric Triglyceride, Polyglyceryl-10 Diisostearate, Hydrogenated Lecithin, Butylene Glycol, Bromelain, Papain, Menadione, Caprylyl Glycol

PURPOSE

Purpose: Exfoliate Dead Skin (Keratin)

WARNINGS

Warnings: 1. In case of having following symptoms after using this product, stop using it immediately. If the symptoms get worse, you need to consult a dermatologist. 1) In case of having problems such as red spots, swelling, itching or irritation during using this product, 2) In case of having the same symptoms above on the part where you put this product, which is exposed to direct sunlight. 2. Do not use it on the part where you have a scar, eczema or dermatitis. 3. For external use only

Keep out of reach of children: Keep out of reach of babies and children.

INDICATIONS & USAGE

Indications & Usage: 1. After face wash & towel dry, apply the exfoliator avoiding eye & lip areas enough to cover entire face. 2. Massage your face in circular movement for about 20-30sec. You can see the dead skin falling out while the formula changes to rubber like gomage. 3. Rinse thoroughly with clean water. Follow with your skin care items.

DOSAGE & ADMINISTRATION

Dosage & Administration: Take an adequate amount of this product.